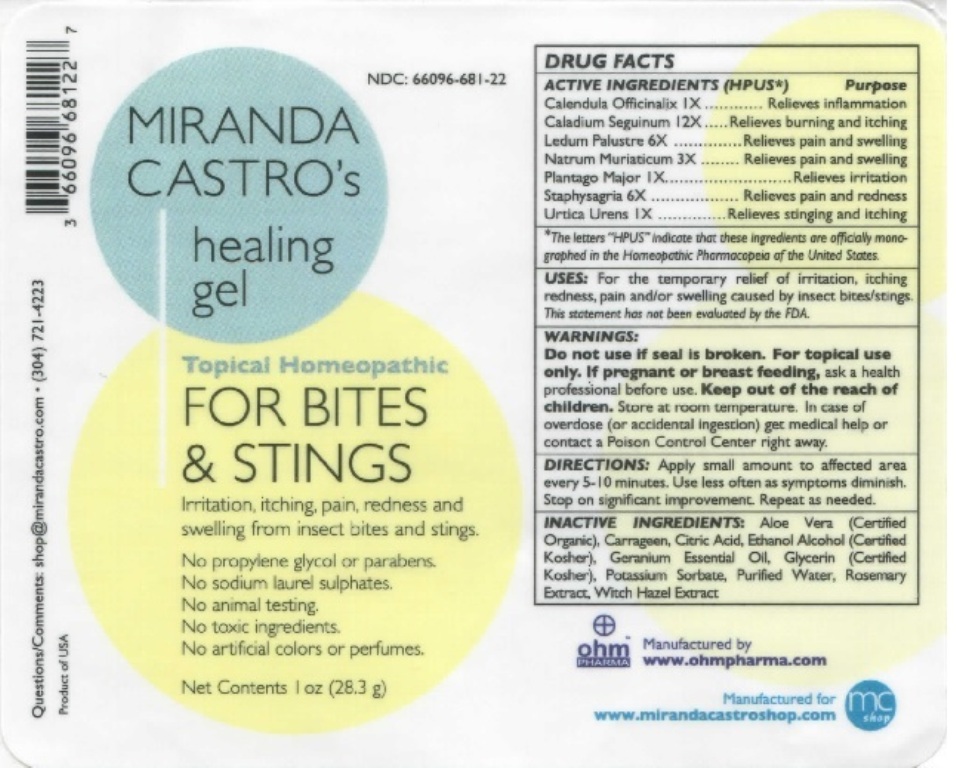 DRUG LABEL: Miranda Castros Healing Gel for Bites and Stings
NDC: 66096-681 | Form: GEL
Manufacturer: OHM PHARMA INC.
Category: homeopathic | Type: HUMAN OTC DRUG LABEL
Date: 20221202

ACTIVE INGREDIENTS: CALENDULA OFFICINALIS FLOWERING TOP 1 [hp_X]/28.3 g; DIEFFENBACHIA SEGUINE 12 [hp_X]/28.3 g; RHODODENDRON TOMENTOSUM LEAFY TWIG 6 [hp_X]/28.3 g; SODIUM CHLORIDE 3 [hp_X]/28.3 g; PLANTAGO MAJOR 1 [hp_X]/28.3 g; DELPHINIUM STAPHISAGRIA SEED 6 [hp_X]/28.3 g; URTICA URENS 1 [hp_X]/28.3 g
INACTIVE INGREDIENTS: ALOE VERA LEAF; CHONDRUS CRISPUS; CITRIC ACID MONOHYDRATE; ALCOHOL; GERANIUM OIL, ALGERIAN TYPE; GLYCERIN; POTASSIUM SORBATE; WATER; ROSEMARY; WITCH HAZEL

Miranda Castros Healing Gel

ACTIVE INGREDIENTS (HPUS*) PURPOSE

Calendula Officinalis 1X ................. Relieves inflammation

Caladium Seguinum 12X ..... Relieves burning and itching

Ledum Palustre 6X ................ Relieves pain and swelling

Natrum Muriaticum 3X ........... Relieves pain and swelling

Plantago Major 1X ............................... Relieves irritation

Staphysagria 6X .................... Relieves pain and redness

Urtica Urens 1X .................. Relieves stinging and itching

*The letters "HPUS" indicate that these ingredients are officially monographed in the Homeopathic Pharmacopeia of the United States.

INDICATIONS AND USAGE

USES: For the temporary relief of irritation, itching redness, pain and/or swelling caused by insect bites/stings.

This statement has not been evaluated by the FDA.

WARNINGS

WARNINGS: For topical use only. If pregnant or breast feeding, ask a health professional before use. Store at room temperature. In case of overdose (or accidental ingestion) get medical help or contact a Poison Control Center right away.

- KEEP OUT OF THE REACH OF CHILDREN.

DOSAGE AND ADMINISTRATION

DIRECTIONS: Apply small amount to affected area every 5-10 minutes. Use less often as symptoms diminish. Stop on significant improvement. Repeat as needed.

Do not use if seal is broken.

INACTIVE INGREDIENT

Inactive Ingredients: Aloe Vera (Certified Organic), Carrageen, Citric Acid, Ethanol Alcohol (Certified Kosher), Geranium Essential Oil, Glycerin (Certified Kosher), Potassium Sorbate, Purified Water, Rosemary Extract, Witch Hazel Extract.

QUESTIONS

Manufactured by www.ohmpharma.com

Manufactured for www.mirandacastroshop.com

PACKAGE LABEL

NDC: 66096-681-22

MIRANDA CASTRO'S healing gel

Topical Homeopathic

FOR BITES AND STINGS

Irritation, itching, pain, redness and swelling from insect bites and stings.

No Propylene glycol or parabens.

No sodium laurel sulphates.

No animal testing.

No toxic ingredients.

No artificial colors or perfumes.

Net Contents 1 oz (28.3 g)

PURPOSE

Irritation, itching, pain, redness and swelling from insect bites and stings.